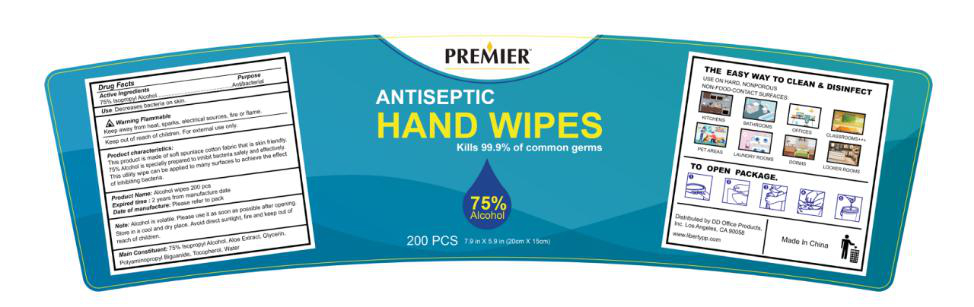 DRUG LABEL: Alcohol Wipes
NDC: 54237-017 | Form: CLOTH
Manufacturer: Guangzhou Daieme Cosmetic Co,.Ltd
Category: otc | Type: HUMAN OTC DRUG LABEL
Date: 20200714

ACTIVE INGREDIENTS: ISOPROPYL ALCOHOL 720 mL/200 1
INACTIVE INGREDIENTS: TOCOPHEROL; GLYCERIN; POLYAMINOPROPYL BIGUANIDE; WATER; ALOE

DOSAGE AND ADMINISTRATION

Please use it as soon as possible after opening Place it in a cool and dry place

INACTIVE INGREDIENT

Aloe Extract, Glycerin,Polyaminopropyl Biguanide,Tocopherol, Water

INDICATIONS AND USAGE

Open the package, pull out a paper towel, wipe back and forth between palms

ACTIVE INGREDIENT

Isopropyl Alcohol

keep out of reach of children

PURPOSE

Disinfection
Sterilization
No Rinseing

WARNINGS

Alcohol is volatile ,Please use it as soon as possible after opening Place it in a cool and dry place, avoid direct sunlight and fire,and avoid children eating by mistake Please keep out of the reach of children, Avoid contact with eyes and damaged skin.